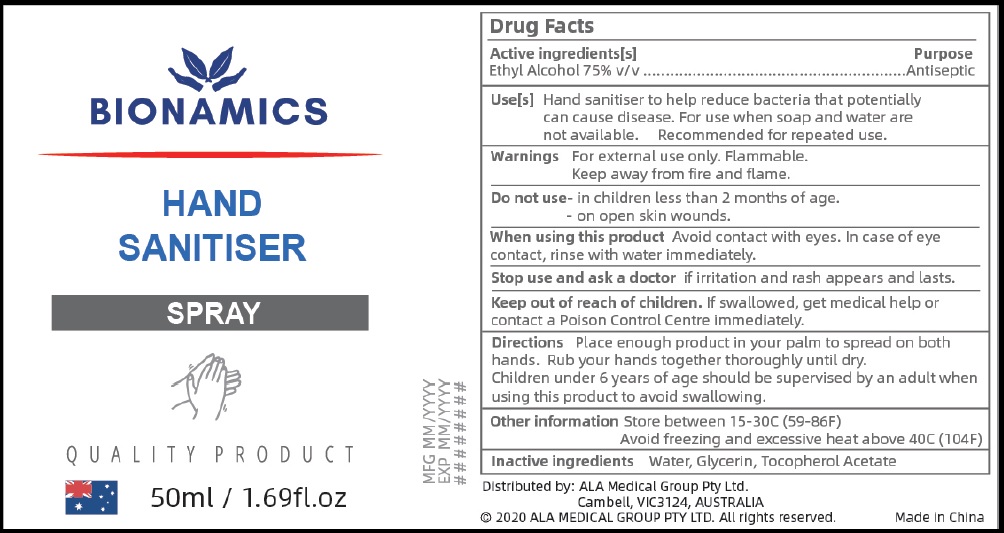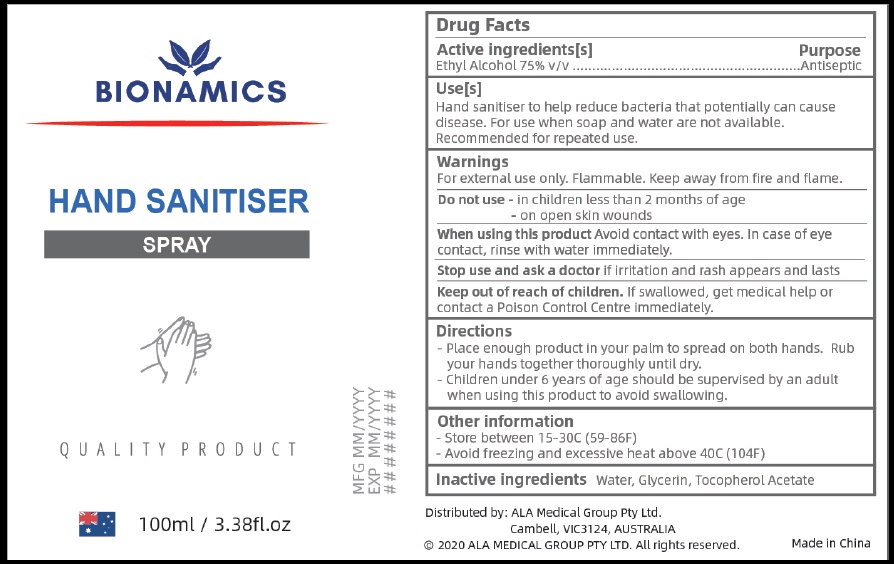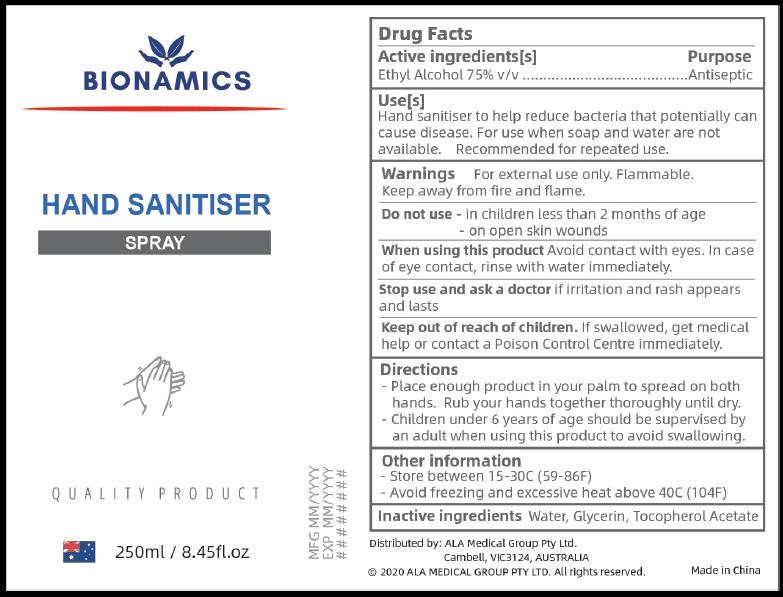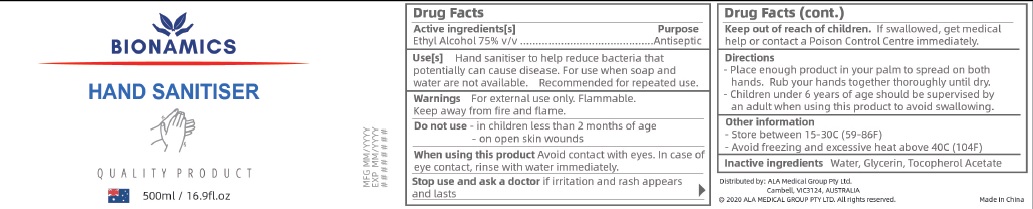 DRUG LABEL: BIONAMICS
NDC: 74198-002 | Form: SPRAY
Manufacturer: ALA MEDICAL GROUP PTY LTD
Category: otc | Type: HUMAN OTC DRUG LABEL
Date: 20200327

ACTIVE INGREDIENTS: ALCOHOL 75 mL/100 mL
INACTIVE INGREDIENTS: WATER; GLYCERIN; .ALPHA.-TOCOPHEROL ACETATE

BIONAMICS

Active lngredient

Ethyl Alcohol

Purpose

Antiseptic

Uses

Hand sanitiser to help reduce bacteria that potentially

can cause disease. For use when soap and water are not available.

Recommended for repeated use.

Warnings

For external use only. Flammable.
Keep away from fire and flame.

Do not use - in children less than 2 months of age.
- on open skin wounds.

When usin g this product Avoid contact with eyes. In case of eye
contact, rinse with water immediately.

Stop use and ask a doctor if irritation and rash appears and lasts.

Other information Store between 15-30C (59-86F)
Avoid freezing and excessive heat above 40C (104F)

Directions

- Place enough product in your palm to spread on both hands.
- Rub your hands together thoroughly until dry.
- Children under 6 years of age should be supervised by an adult when using this product to avoid swallowing.

Inactive ingredients

Water, Glycerin, Tocopherol Acetate.

Keep out of re ach of children

If swallowed, get medical help or contact a Poison Control Centre immediately.